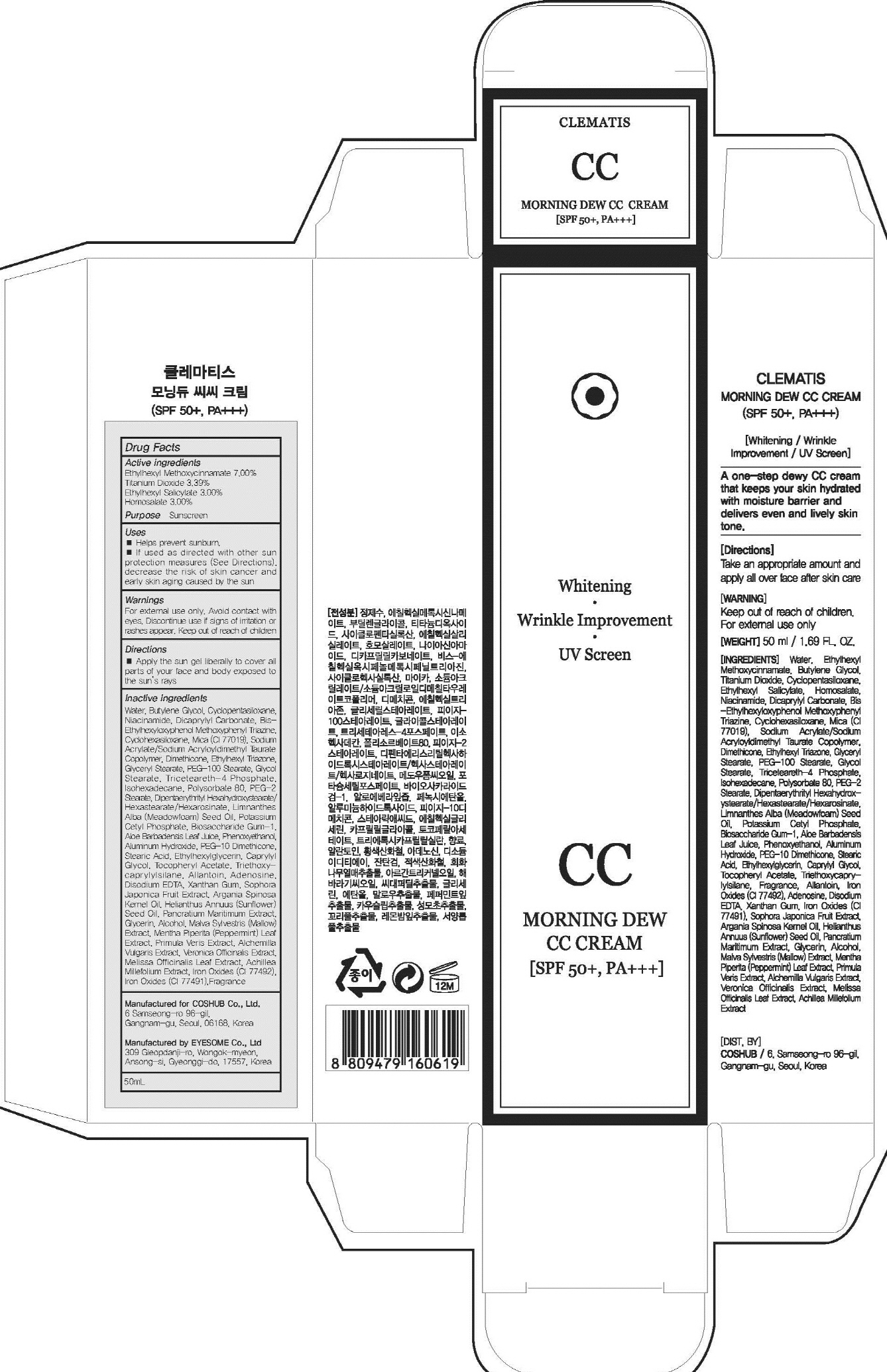 DRUG LABEL: CLEMATIS Morning Dew CC
NDC: 71702-110 | Form: CREAM
Manufacturer: Coshub Co., Ltd.
Category: otc | Type: HUMAN OTC DRUG LABEL
Date: 20170905

ACTIVE INGREDIENTS: Octinoxate 3.50 g/50 mL; Titanium Dioxide 1.69 g/50 mL; Octisalate 1.50 g/50 mL; Homosalate 1.50 g/50 mL
INACTIVE INGREDIENTS: Water; Butylene Glycol

ACTIVE INGREDIENT

Active ingredients: Ethylhexyl Methoxycinnamate 7.00%, Titanium Dioxide 3.39%, Ethylhexyl Salicylate 3.00%, Homosalate 3.00%

INACTIVE INGREDIENT

Inactive ingredients: Water, Butylene Glycol, Cyclopentasiloxane, Niacinamide, Dicaprylyl Carbonate, Bis-Ethylhexyloxyphenol Methoxyphenyl Triazine, Cyclohexasiloxane, Mica (CI 77019), Sodium Acrylate/Sodium Acryloyldimethyl Taurate Copolymer, Dimethicone, Ethylhexyl Triazone, Glyceryl Stearate, PEG-100 Stearate, Glycol Stearate, Triceteareth-4 Phosphate, Isohexadecane, Polysorbate 80, PEG-2 Stearate, Dipentaerythrityl Hexahydroxystearate/Hexastearate/Hexarosinate, Limnanthes Alba (Meadowfoam) Seed Oil, Potassium Cetyl Phosphate, Biosaccharide Gum-1, Aloe Barbadensis Leaf Juice, Phenoxyethanol, Aluminum Hydroxide, PEG-10 Dimethicone, Stearic Acid, Ethylhexylglycerin, Caprylyl Glycol, Tocopheryl Acetate, Triethoxycaprylylsilane, Allantoin, Adenosine, Disodium EDTA, Xanthan Gum, Sophora Japonica Fruit Extract, Argania Spinosa Kernel Oil, Helianthus Annuus (Sunflower) Seed Oil, Pancratium Maritimum Extract, Glycerin, Alcohol, Malva Sylvestris (Mallow) Extract, Mentha Piperita (Peppermint) Leaf Extract, Primula Veris Extract, Alchemilla Vulgaris Extract, Veronica Officinalis Extract, Melissa Officinalis Leaf Extract, Achillea Millefolium Extract, Iron Oxides (CI 77492), Iron Oxides (CI 77491),Fragrance

PURPOSE

Purpose: Sunscreen

WARNINGS

Warnings: For external use only. Avoid contact with eyes. Replace the cap after use. Discontinue use if signs of irritation or rashes appear. Keep out of reach of children.

DESCRIPTION

Uses: - Helps prevent sunburn. - If used as directed with other sun protection measures (See Directions), decrease the risk of skin cancer and early skin aging caused by the sun

Directions: Apply the sun gel liberally to cover all parts of your face and body exposed to the sun's rays.